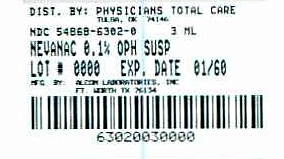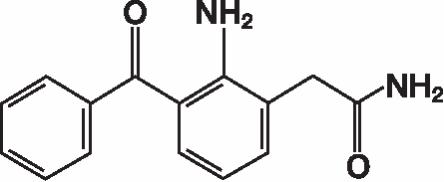 DRUG LABEL: Nevanac
NDC: 54868-6302 | Form: SUSPENSION
Manufacturer: Physicians Total Care, Inc.
Category: prescription | Type: HUMAN PRESCRIPTION DRUG LABEL
Date: 20110831

ACTIVE INGREDIENTS: NEPAFENAC 1 mg/1 mL
INACTIVE INGREDIENTS: MANNITOL; CARBOMER HOMOPOLYMER TYPE B (ALLYL PENTAERYTHRITOL CROSSLINKED); SODIUM CHLORIDE; TYLOXAPOL; EDETATE DISODIUM; BENZALKONIUM CHLORIDE; SODIUM HYDROXIDE; HYDROCHLORIC ACID; WATER

HIGHLIGHTS OF PRESCRIBING INFORMATION

These highlights do not include all the information needed to use nevanac safely and effectively. See full prescribing information for nevanac. nevanac (nepafenac) suspension for ophthalmic use Initial U.S. Approval: 2005

1 INDICATIONS AND USAGE

NEVANAC® ophthalmic suspension is a nonsteroidal, anti-inflammatory prodrug indicated for the treatment of pain and inflammation associated with cataract surgery (1)

2 DOSAGE AND ADMINISTRATION

One drop of NEVANAC® ophthalmic suspension should be applied to the affected eye(s) three-times-daily beginning 1 day prior to cataract surgery, continued on the day of surgery and through the first 2 weeks of the postoperative period. (2)

3 DOSAGE FORMS AND STRENGTHS

Sterile ophthalmic suspension: 0.1% (3)

3 mL in a 4 mL bottle

4 CONTRAINDICATIONS

Hypersensitivity to any of the ingredients in the formula or to other NSAIDS.(4)

5 WARNINGS AND PRECAUTIONS

Increased bleeding time due to increased thrombocyte aggregation (5.1)

Delayed healing (5.2)

Corneal effects including keratitis (5.3)

6 ADVERSE REACTIONS

Most common adverse reactions (5 to 10%) are capsular

opacity, decreased visual acuity, foreign body sensation, increased intraocular pressure, and sticky sensation. (6.1)

To report SUSPECTED ADVERSE REACTIONS, contact Alcon Laboratories, Inc. at 1-800-757-9195 or FDA at 1-800-FDA-1088 or www.fda.gov/medwatch

FULL PRESCRIBING INFORMATION

1 INDICATIONS AND USAGE

NEVANAC® ophthalmic suspension is indicated for the treatment of pain and inflammation associated with cataract surgery.

2 DOSAGE AND ADMINISTRATION

Enter section text here

2.1 Recommended Dosing

One drop of NEVANAC® should be applied to the affected eye(s) three-times-daily beginning 1 day prior to cataract surgery, continued on the day of surgery and through the first 2 weeks of the postoperative period.

2.2 Use with Other Topical Ophthalmic Medications

NEVANAC® may be administered in conjunction with other topical ophthalmic medications such as beta-blockers, carbonic anhydrase inhibitors, alpha-agonists, cycloplegics, and mydriatics.

3 DOSAGE FORMS AND STRENGTHS

Sterile ophthalmic suspension: 0.1%

3 mL in a 4 mL bottle

4 CONTRAINDICATIONS

NEVANAC® is contraindicated in patients with previously demonstrated hypersensitivity to any of the ingredients in the formula or to other NSAIDs.

5 WARNINGS AND PRECAUTIONS

Enter section text here

5.1 Increased Bleeding Time

With some nonsteroidal anti-inflammatory drugs including NEVANAC®, there exists the potential for increased bleeding time due to interference with thrombocyte aggregation. There have been reports that ocularly applied nonsteroidal anti-inflammatory drugs may cause increased bleeding of ocular tissues (including hyphemas) in conjunction with ocular surgery.

It is recommended that NEVANAC® ophthalmic suspension be used with caution in patients with known bleeding tendencies or who are receiving other medications which may prolong bleeding time.

5.2 Delayed Healing

Topical nonsteroidal anti-inflammatory drugs (NSAIDs) including NEVANAC®, may slow or delay healing. Topical corticosteroids are also known to slow or delay healing. Concomitant use of topical NSAIDs and topical steroids may increase the potential for healing problems.

5.3 Corneal Effects

Use of topical NSAIDs may result in keratitis. In some susceptible patients, continued use of topical NSAIDs may result in epithelial breakdown, corneal thinning, corneal erosion, corneal ulceration or corneal perforation. These events may be sight threatening. Patients with evidence of corneal epithelial breakdown should immediately discontinue use of topical NSAIDs including NEVANAC® and should be closely monitored for corneal health.

Postmarketing experience with topical NSAIDs suggests that patients with complicated ocular surgeries, corneal denervation, corneal epithelial defects, diabetes mellitus, ocular surface diseases (e.g., dry eye syndrome), rheumatoid arthritis, or repeat ocular surgeries within a short period of time may be at increased risk for corneal adverse events which may become sight threatening. Topical NSAIDs should be used with caution in these patients.

Postmarketing experience with topical NSAIDs also suggests that use more than 1 day prior to surgery or use beyond 14 days post surgery may increase patient risk and severity of corneal adverse events.

5.4 Contact Lens Wear

NEVANAC® should not be administered while using contact lenses.

6 ADVERSE REACTIONS

Because clinical studies are conducted under widely varying conditions, adverse reaction rates observed in the clinical studies of a drug cannot be directly compared to the rates in the clinical studies of another drug and may not reflect the rates observed in practice.

6.1 Ocular Adverse Reactions

The most frequently reported ocular adverse events following cataract surgery were capsular opacity, decreased visual acuity, foreign body sensation, increased intraocular pressure, and sticky sensation. These events occurred in approximately 5 to 10% of patients.

Other ocular adverse events occurring at an incidence of approximately 1 to 5% included conjunctival edema, corneal edema, dry eye, lid margin crusting, ocular discomfort, ocular hyperemia, ocular pain, ocular pruritus, photophobia, tearing and vitreous detachment.

Some of these events may be the consequence of the cataract surgical procedure.

6.2 Non-Ocular Adverse Reactions

Non-ocular adverse events reported at an incidence of 1 to 4% included headache, hypertension, nausea/vomiting, and sinusitis.

8 USE IN SPECIFIC POPULATIONS

Enter section text here

8.1 Pregnancy

Teratogenic Effects.

Pregnancy Category C: Reproduction studies performed with nepafenac in rabbits and rats at oral doses up to 10 mg/kg/day have revealed no evidence of teratogenicity due to nepafenac, despite the induction of maternal toxicity. At this dose, the animal plasma exposure to nepafenac and amfenac was approximately 260 and 2400 times human plasma exposure at the recommended human topical ophthalmic dose for rats and 80 and 680 times human plasma exposure for rabbits, respectively. In rats, maternally toxic doses ≥ 10 mg/kg were associated with dystocia, increased postimplantation loss, reduced fetal weights and growth, and reduced fetal survival.

Nepafenac has been shown to cross the placental barrier in rats. There are no adequate and well-controlled studies in pregnant women. Because animal reproduction studies are not always predictive of human response, NEVANAC® should be used during pregnancy only if the potential benefit justifies the potential risk to the fetus.

Non-teratogenic Effects.

Because of the known effects of prostaglandin biosynthesis inhibiting drugs on the fetal cardiovascular system (closure of the ductus arteriosus), the use of NEVANAC® during late pregnancy should be avoided.

8.3 Nursing Mothers

NEVANAC® is excreted in the milk of lactating rats. It is not known whether this drug is excreted in human milk. Because many drugs are excreted in human milk, caution should be exercised when NEVANAC® ophthalmic suspension is administered to a nursing woman.

8.4 Pediatric Use

The safety and effectiveness of NEVANAC® in pediatric patients below the age of 10 years have not been established.

8.5 Geriatric Use

No overall differences in safety and effectiveness have been observed between elderly and younger patients.

11 DESCRIPTION

NEVANAC® (nepafenac ophthalmic suspension) 0.1% is a sterile, topical, nonsteroidal anti-inflammatory (NSAID) prodrug for ophthalmic use. Each mL of NEVANAC® suspension contains 1 mg of nepafenac. Nepafenac is designated chemically as 2-amino-3-benzoylbenzeneacetamide with an empirical formula of C15H14N2O2. The structural formula of nepafenac is:

Nepafenac is a yellow crystalline powder. The molecular weight of nepafenac is 254.28. NEVANAC®ophthalmic suspension is supplied as a sterile, aqueous 0.1% suspension with a pH approximately of 7.4.

The osmolality of NEVANAC®ophthalmic suspension is approximately 305 mOsmol/kg.

Each mL of NEVANAC® contains: Active: nepafenac 0.1% Inactives: mannitol, carbomer 974P, sodium chloride, tyloxapol, edetate disodium, benzalkonium chloride 0.005% (preservative), sodium hydroxide and/or hydrochloric acid to adjust pH and purified water, USP.

12 CLINICAL PHARMACOLOGY

Enter section text here

12.1 Mechanism of Action

After topical ocular dosing, nepafenac penetrates the cornea and is converted by ocular tissue hydrolases to amfenac, a nonsteroidal anti-inflammatory drug. Amfenac is thought to inhibit the action of prostaglandin H synthase (cyclooxygenase), an enzyme required for prostaglandin production.

12.3 Pharmacokinetics

Low but quantifiable plasma concentrations of nepafenac and amfenac were observed in the majority of subjects 2 and 3 hours postdose, respectively, following bilateral topical ocular three-times-daily dosing of nepafenac ophthalmic suspension, 0.1%. The mean steady-state Cmax for nepafenac and for amfenac were 0.310 ± 0.104 ng/ml and 0.422 ± 0.121 ng/ml, respectively, following ocular administration.

Nepafenac at concentrations up to 300 ng/mL did not inhibit the in vitro metabolism of 6 specific marker substrates of cytochrome P450 (CYP) isozymes (CYP1A2, CYP2C9, CYP2C19, CYP2D6, CYP2E1, and CYP3A4). Therefore, drug-drug interactions involving CYP mediated metabolism of concomitantly administered drugs are unlikely. Drug-drug interactions mediated by protein binding are also unlikely.

13 NONCLINICAL TOXICOLOGY

Enter section text here

13.1 Carcinogenesis, Mutagenesis, Impairment of Fertility

Nepafenac has not been evaluated in long-term carcinogenicity studies. Increased chromosomal aberrations were observed in Chinese hamster ovary cells exposed in vitro to nepafenac suspension. Nepafenac was not mutagenic in the Ames assay or in the mouse lymphoma forward mutation assay. Oral doses up to 5,000 mg/kg did not result in an increase in the formation of micronucleated polychromatic erythrocytes in vivo in the mouse micronucleus assay in the bone marrow of mice.

Nepafenac did not impair fertility when administered orally to male and female rats at 3 mg/kg (approximately 90 and 380 times the plasma exposure to the parent drug, nepafenac, and the active metabolite, amfenac, respectively, at the recommended human topical ophthalmic dose).

14 CLINICAL STUDIES

In two double-masked, randomized clinical trials in which patients were dosed three-times-daily beginning one day prior to cataract surgery, continued on the day of surgery and for the first two weeks of the postoperative period, NEVANAC® ophthalmic suspension demonstrated clinical efficacy, compared to its vehicle in treating postoperative inflammation.

Patients treated with NEVANAC® ophthalmic suspension were less likely to have ocular pain and measurable signs of inflammation (cells and flare) in the early postoperative period through the end of treatment than those treated with its vehicle.

For ocular pain in both studies a significantly higher percentage of patients (approximately 80%) in the nepafenac group reported no ocular pain on the day following cataract surgery (Day 1) compared to those in the vehicle group (approximately 50%).

Results from clinical studies indicated that NEVANAC® has no significant effect upon intraocular pressure; however, changes in intraocular pressure may occur following cataract surgery.

16 HOW SUPPIED/STORAGE AND HANDLING

NEVANAC® (nepafenac ophthalmic suspension) is supplied in a natural, oval, low density polyethylene DROP-TAINER® dispenser with a natural low density polyethylene dispensing plug and gray polypropylene cap. Tamper evidence is provided with a shrink band around the closure and neck area of the package.

3 mL in 4 mL bottle NDC 54868-6302-0

Storage: Store at 2 - 25°C (36 - 77°F).

17 PATIENT COUNSELING INFORMATION

Enter section text here

17.1 Slow or Delayed Healing

Patients should be informed of the possibility that slow or delayed healing may occur while using nonsteroidal anti-inflammatory drugs (NSAIDs).

17.2 Avoiding Contamination of the Product

Patients should be instructed to avoid allowing the tip of the dispensing container to contact the eye or surrounding structures because this could cause the tip to become contaminated by common bacteria known to cause ocular infections. Serious damage to the eye and subsequent loss of vision may result from using contaminated solutions.

17.3 Contact Lens Wear

NEVANAC® should not be administered while wearing contact lens.

17.4 Intercurrent Ocular Conditions

Patients should be advised that if they develop an intercurrent ocular condition (e.g., trauma, or infection) or have ocular surgery, they should immediately seek their physician's advice concerning the continued use of the multi-dose container.

17.5 Concomitant Topical Ocular Therapy

If more than one topical ophthalmic medication is being used, the medicines must be administered at least 5 minutes apart.

17.6 Shake Well Before Use

Patients should be advised to shake the bottle well.

U.S. Patent No; 5,475,034

ALCON®

ALCON LABORATORIES, INC.

Fort Worth, Texas 76134 USA

© 2007 Alcon, Inc.

Additional barcode labeling by:
Physicians Total Care, Inc.
Tulsa, OK 74146

PRINCIPAL DISPLAY PANEL

NEVANAC® (nepafenac ophthalmic suspension)

NDC 54868-6302-0

3 mL